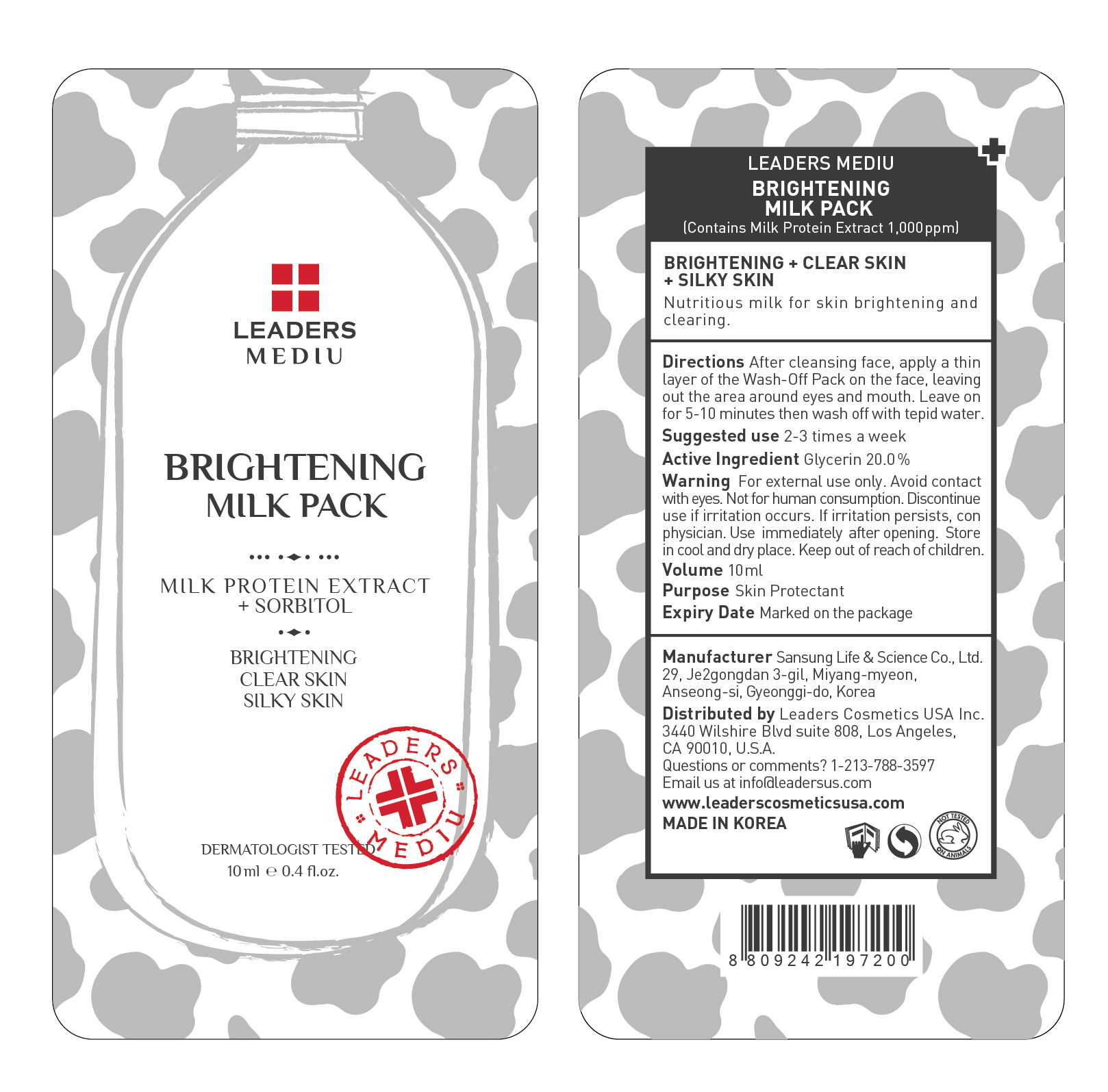 DRUG LABEL: LEADERS MEDIU BRIGHTENING MILK PACK
NDC: 69424-440 | Form: GEL
Manufacturer: SANSUNG LIFE & SCIENCE CO., LTD.
Category: otc | Type: HUMAN OTC DRUG LABEL
Date: 20160201

ACTIVE INGREDIENTS: Glycerin 2.0 g/10 mL
INACTIVE INGREDIENTS: Water; Sorbitol

ACTIVE INGREDIENT

Active Ingredient: Glycerin 20.0%

INACTIVE INGREDIENT

Inactive Ingredients: Water, Sorbitol, Titanium Dioxide, Alcohol, Hydroxyethyl Acrylate/Sodium Acryloyldimethyl Taurate Copolymer, Squalane, PVP, Ethyl Hexanediol, Polysorbate 60, Panthenol, Arginine, Carbomer, Fragrance, Glyceryl Caprylate, Milk Protein Extract, Triethoxycaprylylsilane, Alumina

PURPOSE

Purpose: Skin Protectant

WARNINGS

Warnings: For external use only. Avoid contact with eyes. Not for human consumption. Discontinue use if irritation occurs. If irritation persists, consult a physician.

Use immediately after opening. Store in cool and dry place. Keep out of reach of children.

Directions

Directions: After cleansing face, apply a thin layer of the Wash-Off Pack on the face, leaving out the area around eyes and mouth. Leave on for 5-10 minutes then wash off with tepid water. *Suggested use is 2-3 times a week

KEEP OUT OF REACH OF CHILDREN

Directions

Directions: After cleansing face, apply a thin layer of the Wash-Off Pack on the face, leaving out the area around eyes and mouth. Leave on for 5-10 minutes then wash off with tepid water. *Suggested use is 2-3 times a week